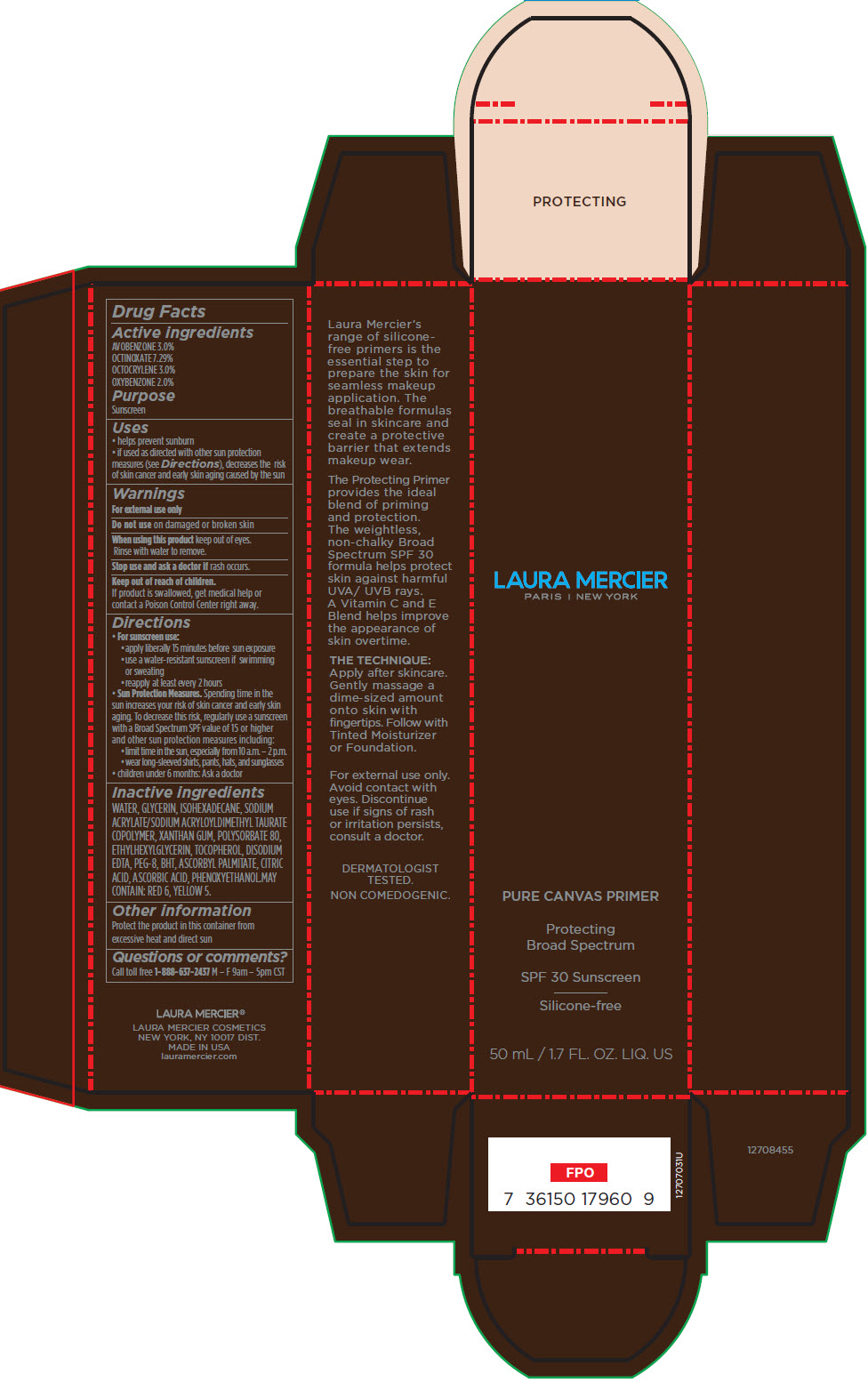 DRUG LABEL: Laura Mercier Pure Canvas Primer Protecting Broad Spectrum SPF 30 Sunscreen
NDC: 82761-055 | Form: CREAM
Manufacturer: Laura Mercier US Buyer LLC
Category: otc | Type: HUMAN OTC DRUG LABEL
Date: 20231004

ACTIVE INGREDIENTS: OCTINOXATE 3.681 g/50 mL; OCTOCRYLENE 1.515 g/50 mL; AVOBENZONE 1.515 g/50 mL; OXYBENZONE 1.01 g/50 mL
INACTIVE INGREDIENTS: WATER; GLYCERIN; ISOHEXADECANE; SODIUM ACRYLATE/SODIUM ACRYLOYLDIMETHYLTAURATE COPOLYMER (4000000 MW); XANTHAN GUM; POLYSORBATE 80; ETHYLHEXYLGLYCERIN; .ALPHA.-TOCOPHEROL; EDETATE DISODIUM; POLYETHYLENE GLYCOL 400; BUTYLATED HYDROXYTOLUENE; ASCORBYL PALMITATE; CITRIC ACID MONOHYDRATE; ASCORBIC ACID; PHENOXYETHANOL; D&C RED NO. 6; FD&C YELLOW NO. 5

Laura Mercier Pure Canvas Primer Protecting Broad Spectrum SPF 30 Sunscreen

Drug Facts

Active ingredients

AVOBENZONE 3.0%

OCTINOXATE 7.29%

OCTOCRYLENE 3.0%

OXYBENZONE 2.0%

Purpose

Sunscreen

Uses

- helps prevent sunburn
- if used as directed with other sun protection measures (see Directions), decreases the risk of skin cancer and early skin aging caused by the sun

Warnings

For external use only

Do not use on damaged or broken skin

When using this product keep out of eyes. Rinse with water to remove.

Stop use and ask a doctor if rash occurs.

Keep out of reach of children.

If product is swallowed, get medical help or contact a Poison Control Center right away.

Directions

- For sunscreen use:
  - apply liberally 15 minutes before sun exposure
  - use a water-resistant sunscreen if swimming or sweating
  - reapply at least every 2 hours
- Sun Protection Measures. Spending time in the sun increases your risk of skin cancer and early skin aging. To decrease this risk, regularly use a sunscreen with a Broad Spectrum SPF value of 15 or higher and other sun protection measures including:
  - limit time in the sun, especially from 10 a.m. – 2 p.m.
  - wear long-sleeved shirts, pants, hats, and sunglasses
- children under 6 months: Ask a doctor

Inactive ingredients

WATER, GLYCERIN, ISOHEXADECANE, SODIUM ACRYLATE/SODIUM ACRYLOYLDIMETHYL TAURATE COPOLYMER, XANTHAN GUM, POLYSORBATE 80, ETHYLHEXYLGLYCERIN, TOCOPHEROL, DISODIUM EDTA, PEG-8, BHT, ASCORBYL PALMITATE, CITRIC ACID, ASCORBIC ACID, PHENOXYETHANOL.MAY CONTAIN: RED 6, YELLOW 5.

Other information

Protect the product in this container from excessive heat and direct sun

Questions or comments?

Call toll free 1-888-637-2437 M – F 9am – 5pm CST

PRINCIPAL DISPLAY PANEL - 50 mL Tube Carton

LAURA MERCIER
PARIS | NEW YORK

PURE CANVAS PRIMER

Protecting
Broad Spectrum

SPF 30 Sunscreen

Silicone-free

50 mL / 1.7 FL. OZ. LIQ. US